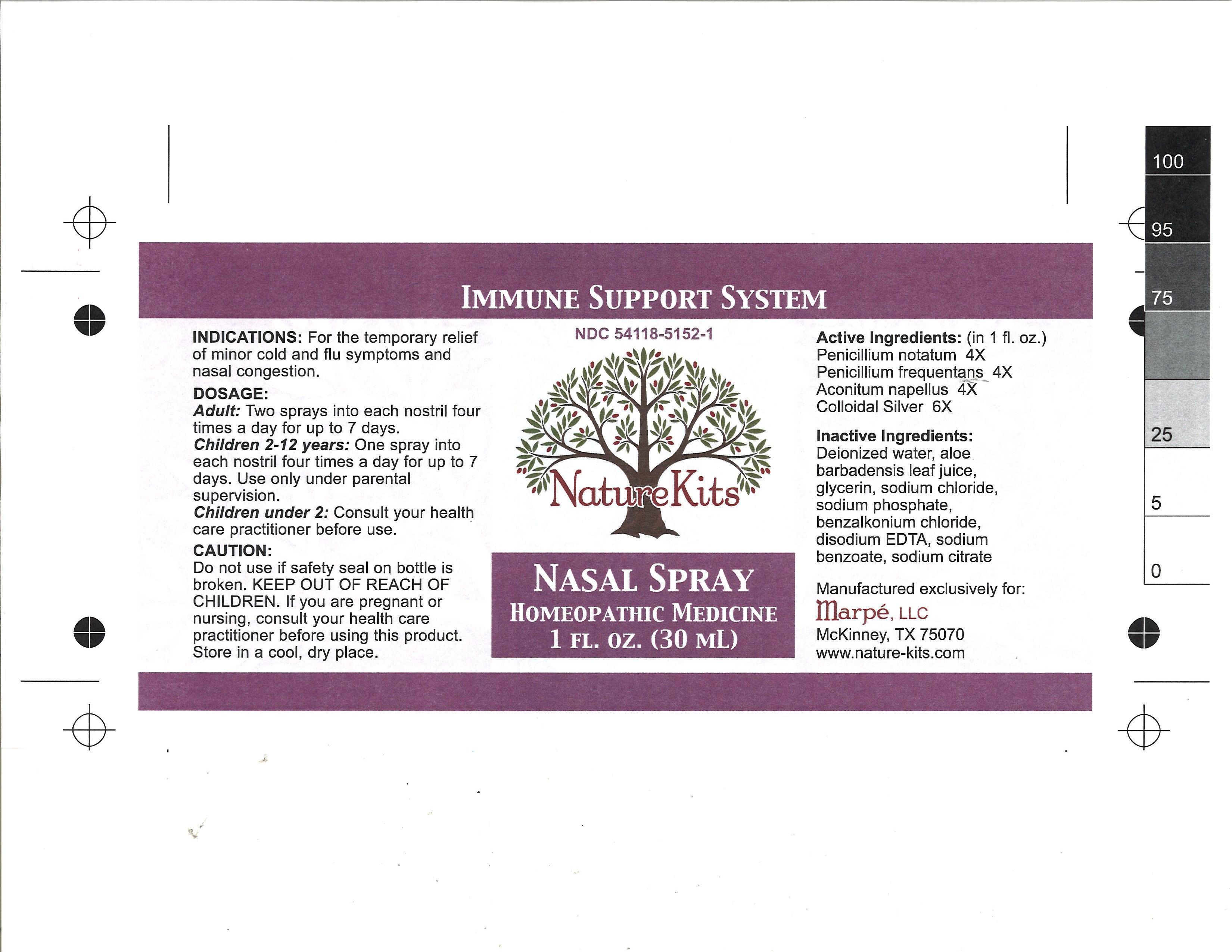 DRUG LABEL: Immune Support System
                
NDC: 54118-5152 | Form: SPRAY
Manufacturer: ABCO Laboratories, Inc.
Category: homeopathic | Type: HUMAN OTC DRUG LABEL
Date: 20120906

ACTIVE INGREDIENTS: PENICILLIUM CHRYSOGENUM VAR. CHRYSOGENUM 4 [hp_X]/30 mL; PENICILLIUM GLABRUM 4 [hp_X]/30 mL; ACONITUM NAPELLUS 4 [hp_X]/30 mL; SILVER 6 [hp_X]/30 mL
INACTIVE INGREDIENTS: SODIUM CITRATE; ALOE VERA LEAF; GLYCERIN; SODIUM CHLORIDE; SODIUM PHOSPHATE; BENZALKONIUM CHLORIDE; EDETATE DISODIUM; SODIUM BENZOATE

Immune Support System Nasal Spray

ACTIVE INGREDIENT

Image of bottle label
label.jpg
Active ingredients:
Penicillium notatum 4X
Penicillium frequentans 4X
Aconitum napellus 4X
Colloidal silver 6X

PURPOSE

Indications: For the temporary relief of minor cold and flu symptoms and nasal congestion

Keep out of reach of children

INDICATIONS AND USAGE

Indications: For temporary relief of minor cold and flu symptoms and nasal congestion.

Dosage:
Adult: Two sprays into each nostril 4 times a day for up to 7 days
Children 2 - 12 years: 1 spray into each nostril 4 times a day for up to 7 days
Children under 2: Consult your pediatrician before use

Do not use if safety seal on bottle is broken. If you are pregnant or nursing, consult your health care practitioner before use.

Keep out of reach of children.

Dosage:
Adult: Two sprays into each nostril 4 times a day for up to 7 days
Children 2 - 12 years: 1 spray into each nostril 4 times a day for up to 7 days
Children under 2: Consult your pediatrician before use

Inactive ingredients:

Deionized water

Aloe barbadensis leaf juice

Glycerin

Sodium chloride

Sodium phosphate

Benzalkonium chloride

Disodium EDTA

Sodium benzoate

Sodium citrate

label.jpg
image of bottle label